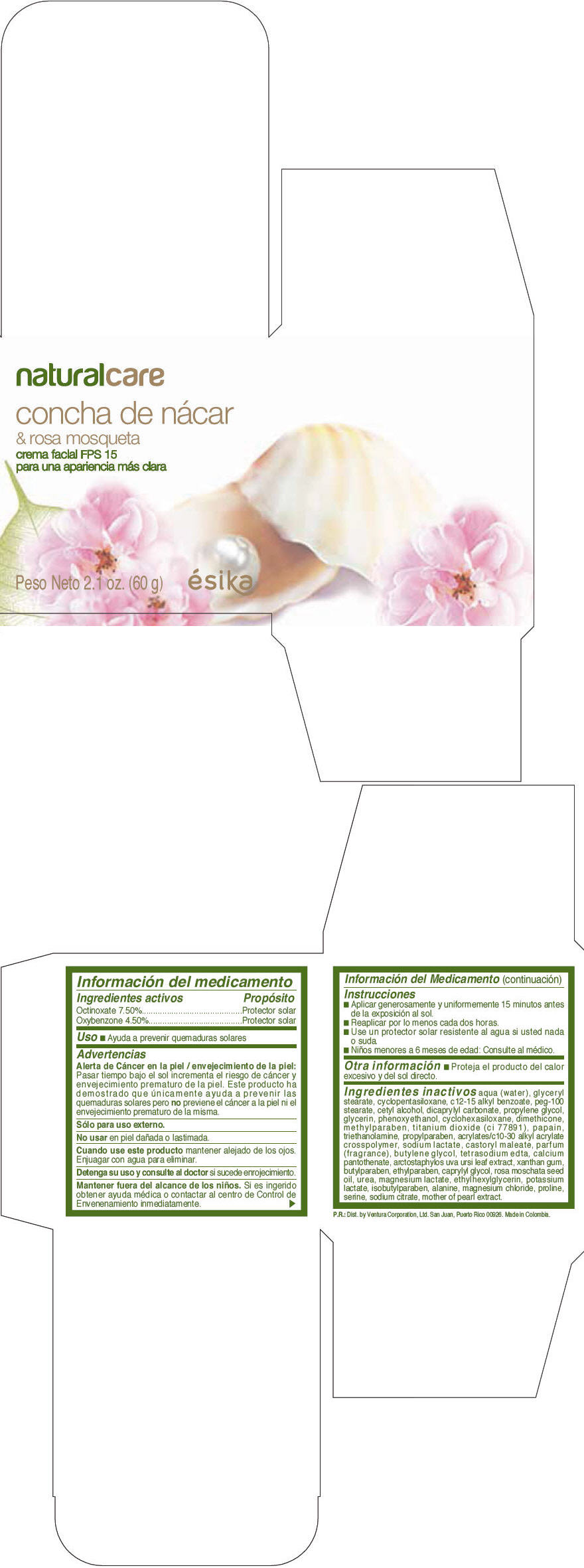 DRUG LABEL: ESIKA NATURAL CARE CONCHA DE NACAR AND ROSA MOSQUETA facial FPS 15
NDC: 13537-199 | Form: CREAM
Manufacturer: Ventura Corporation LTD
Category: otc | Type: HUMAN OTC DRUG LABEL
Date: 20140219

ACTIVE INGREDIENTS: Octinoxate 0.075 g/1 g; Oxybenzone 0.045 g/1 g
INACTIVE INGREDIENTS: WATER; GLYCERYL MONOSTEARATE; CYCLOMETHICONE 5; ALKYL (C12-15) BENZOATE; PEG-100 STEARATE; CETYL ALCOHOL; DICAPRYLYL CARBONATE; PROPYLENE GLYCOL; GLYCERIN; PHENOXYETHANOL; CYCLOMETHICONE 6; DIMETHICONE; METHYLPARABEN; TITANIUM DIOXIDE; PAPAIN; TROLAMINE; PROPYLPARABEN; SODIUM LACTATE; CASTORYL MALEATE; BUTYLENE GLYCOL; EDETATE SODIUM; CALCIUM PANTOTHENATE; ARCTOSTAPHYLOS UVA-URSI LEAF; XANTHAN GUM; BUTYLPARABEN; ETHYLPARABEN; CAPRYLYL GLYCOL; ROSA MOSCHATA SEED OIL; UREA; MAGNESIUM LACTATE; ETHYLHEXYLGLYCERIN; POTASSIUM LACTATE; ISOBUTYLPARABEN; ALANINE; MAGNESIUM CHLORIDE; PROLINE; SERINE; SODIUM CITRATE

ESIKA NATURAL CARE CONCHA DE NÁCAR & ROSA MOSQUETA crema facial FPS 15

Información del medicamento

ACTIVE INGREDIENT

PURPOSE

Ingedientes activos | Propósito
Octinoxate (7.5%) | Protector solar
Oxybenzone (4.5%) | Protector solar

Uso

- Ayuda a prevenir las quemaduras solares

Advertencias

- Alerta de Cáncer en la piel /envejecimiento de la piel: Pasar tiempo bajo elsol incrementa el riesgo de cáncer y envejecimiento prematuro de la piel. Este productoha demostrado que únicamente ayuda a prevenir las quemaduras solares pero no previene el cáncer a la piel ni el envejecimiento prematuro de la misma.

- Sólo para uso externo.

DO NOT USE

- No usar en piel dañada o lastimada.

WHEN USING

- Cuando use este producto mantener alejado de los ojos. Enjuagar con agua para eliminar.

STOP USE

- Detenga su uso y consulte al doctor si sucede enrojecimiento.

KEEP OUT OF REACH OF CHILDREN

- Mantener fuera del alcance de los niños. Si es ingerido obtener ayuda médica o contactar al centro de Control de Envenenamiento inmediatamente.

Instrucciones

- Aplicar generosamente y uniformemente 15 minutos antes de la exposición al sol.
- Reaplizar por lo menos cada dos horas.
- Use un protector solar resistente al agua si usted nada o suda.
- Niños menores a 6 meses de edad: Consulte al médico.

Otra información

- Proteja el producto del calor excesivo y del sol directo.

Ingredientes inactivos

AQUA (WATER), GLYCERYL STEARATE, CYCLOPENTASILOXANE, C12-15 ALKYL BENZOATE, PEG-100 STEARATE, CETYL ALCOHOL, DICAPRYLYL CARBONATE, PROPYLENE GLYCOL, GLYCERIN, PHENOXYETHANOL, CYCLOHEXASILOXANE, DIMETHICONE, METHYLPARABEN, TITANIUM DIOXIDE (CI77891), PAPAIN, TRIETHANOLAMINE, PROPYLPARABEN, ACRYLATES/ C10-30 ALKYL ACRYLATE CROSSPOLYMER, SODIUM LACTATE, CASTORYL MALEATE,PARFUM (FRAGRANCE),BUTYLENE GLYCOL, TETRASODIUM EDTA, CALCIUM PANTOTHENATE, ARCTOSTAPHYLOS UVA URSI LEAF EXTRACT, XANTHAN GUM, BUTYLPARABEN, ETHYLPARABEN, CAPRYLYL GLYCOL, ROSA MOSCHATA SEED OIL, UREA, MAGNESIUM LACTATE, ETHYLHEXYLGLYCERIN, POTASSIUM LACTATE, ISOBUTYLPARABEN, ALANINE, MAGNESIUM CHLORIDE, PROLINE, SERINE, SODIUM CITRATE, MOTHER OF PEARL EXTRACT.

P.R.: Dist. by Ventura Corporation, Ltd. San Juan, Puerto Rico 00926.

PRINCIPAL DISPLAY PANEL - 60 g Tube Box

naturalcare

concha de nácar
& rosa mosqueta
crema facial FPS 15
para una apariencia más clara

Peso Neto 2.1 oz. (60 g)
ésika